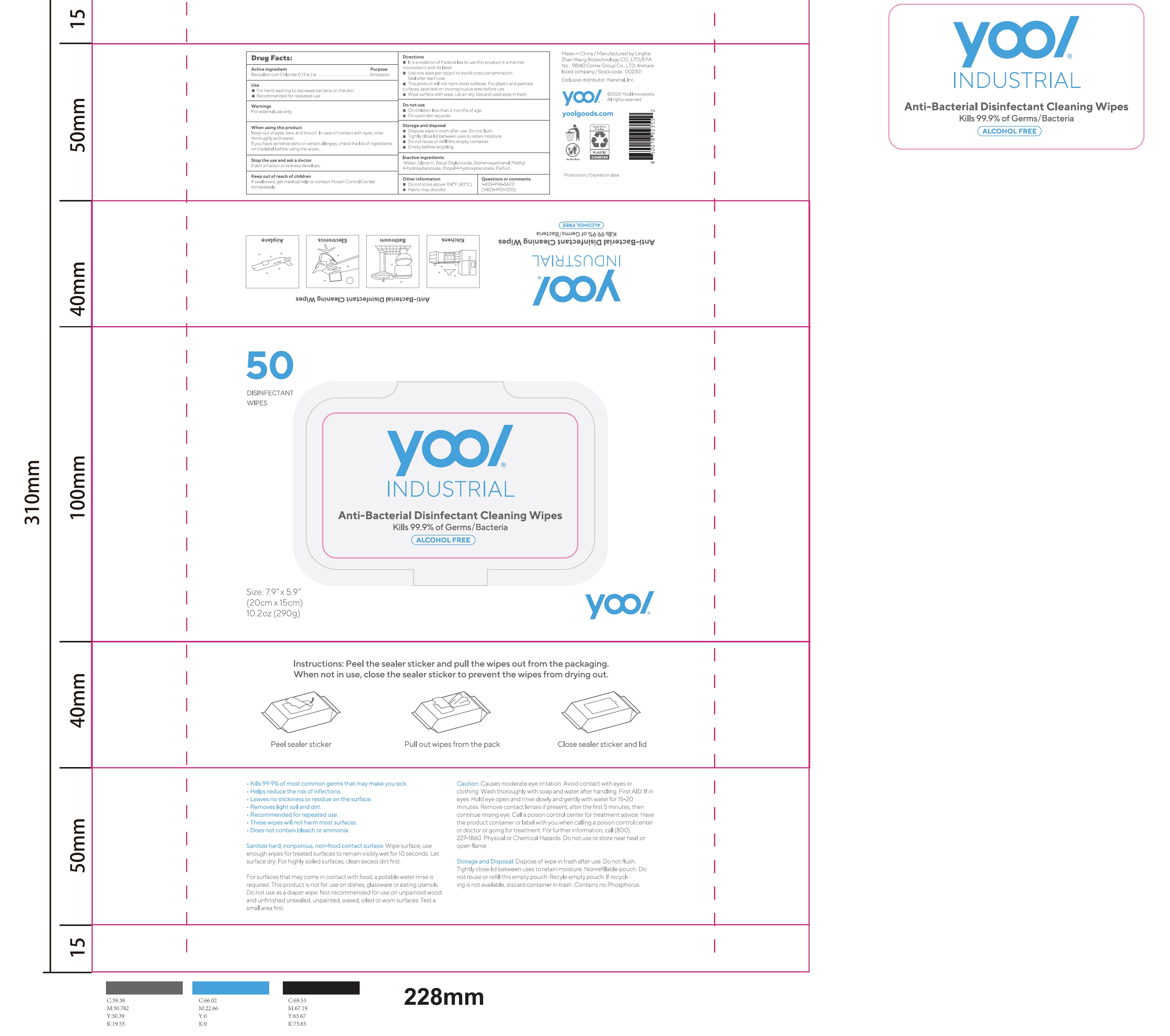 DRUG LABEL: Anti-Bacterial Disinfectant Cleaning Wipes
NDC: 75269-008 | Form: CLOTH
Manufacturer: LINGHAI ZHANWANG BIOTECHNOLOGY CO.,LTD.
Category: otc | Type: HUMAN OTC DRUG LABEL
Date: 20231024

ACTIVE INGREDIENTS: BENZALKONIUM CHLORIDE 0.13 g/100 g
INACTIVE INGREDIENTS: PROPYLPARABEN; FRAGRANCE CLEAN ORC0600327; WATER; GLYCERIN; PHENOXYETHANOL; DECYL GLUCOSIDE; METHYLPARABEN

75269-008 Anti-Bacterial Disinfectant Cleaning Wipes

Active ingredient

Benzalkonium Chloride 0.13 w/w

Purpose

Antiseptic

Use

For hand washing to decrease bacteria on the skin

Recommended for repeated use

Warnings

For external use only.

When using this product

Keep out of eyes, ears, and mouth. In case of contact with eyes, rinse thoroughly with water.

If you have sensitive skins or certain allergies, check the list of ingredients on the label before using the wipes.

Stop the use and ask a doctor

If skin irritation or redness develops.

Keep out of reach of children

If swallowed, get medical help or contact Poison Control Center immediately.

Directions

It is a violation of Federal law to use this product in a manner inconsistent with its label.

Use one wipe per object to avoid cross contamination. Seal after each use.

This product will not harm most surfaces. For plastic and painted surfaces, spot test on inconspicuous area before use.

Wipe surface with wipe. Let air dry. Discard used wipe in trash.

Do not use

On children less than 2 months of age.

On open skin wounds.

Storage and disposal

Dispose wipe in trash after use. Do not flush.

Tightly close lid between uses to retain moisture.

Do not reuse or refill this empty container.

Empty before recycling.

Inactive ingredients

Water, Glycerin, Decyl D-glucoside, 2-phenoxyethanol, Methyl 4-hydroxybenzoate, Propyl 4-hydroxybenzoate, Parfum.

Other information

■ Do not store above 104°F (40°C).

■ Fabric may discolor.

PACKAGE LABEL

50

DISINFECTANT

WIPES

NDC: 75269-008-01